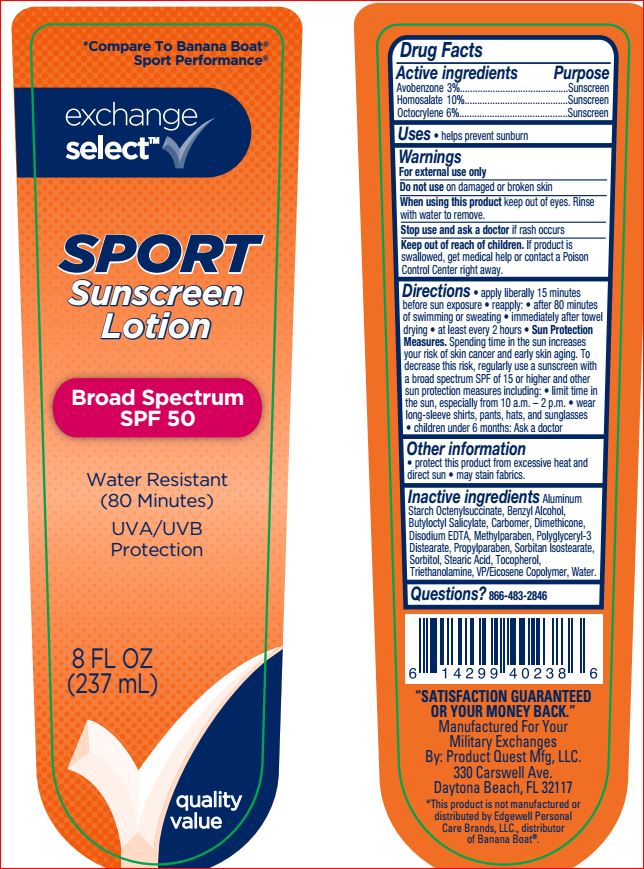 DRUG LABEL: Sunscreen Sport SPF 50
NDC: 55301-778 | Form: LOTION
Manufacturer: Your Military Exchange
Category: otc | Type: HUMAN OTC DRUG LABEL
Date: 20180604

ACTIVE INGREDIENTS: Avobenzone 3 g/100 mL; Homosalate 10 g/100 mL; Octocrylene 6 g/100 mL
INACTIVE INGREDIENTS: Aluminum Starch Octenylsuccinate; Benzyl Alcohol; Butyloctyl Salicylate; CARBOMER HOMOPOLYMER TYPE C (ALLYL PENTAERYTHRITOL CROSSLINKED); Dimethicone; EDETATE DISODIUM; Methylparaben; Polyglyceryl-3 Distearate; Propylparaben; Sorbitan Isostearate; Sorbitol; Stearic Acid; Tocopherol; TROLAMINE; EICOSYL POVIDONE; WATER

Drug Facts

Active ingredients Purpose
Avobenzone 3%.....................................Sunscreen
Homosalate 10%....................................Sunscreen
Octocrylene 6%.....................................Sunscreen

INDICATIONS AND USAGE

Uses • helps prevent sunburn • higher SPF gives more sunburn protection • retains SPF after 80 minutes of activity in the water

Warnings
For external use only
Do not use on damaged or broken skin.
When using this product keep out of eyes.
Rinse with water to remove.
Stop use and ask a doctor if • rash occurs

Keep out of reach of children. If product is swallowed, get medical help or contact a Poison Control Center right away.

DOSAGE AND ADMINISTRATION

Directions • Apply liberally 15 minutes
before sun exposure and as needed. • Reapply:
• after 80 minutes of swimming or sweating
• immediately after towel drying • at least
every 2 hours. • Sun Protection Measures.
Spending time in the sun increases your risk of
skin cancer and early skin aging. To decrease
this risk, regularly use a sunscreen with a
Broad Spectrum SPF value of 15 or higher and
other sun protection measures including:
• limit time in the sun, especially from 10
a.m.-2 p.m. • wear long-sleeved shirts,
pants, hats, and sunglasses. • Children under
6 months of age: ask a doctor.

Other information

• protect the
product in this container from excessive heat
and direct sun • may stain fabrics

Inactive ingredients

Aluminum
Starch Octenylsuccinate, Benzyl Alcohol,
Butyloctyl Salicylate, Carbomer, Dimethicone,
Disodium EDTA, Methylparaben,
Polyglyceryl-3 Distearate, Propylparaben,
Sorbitan Isostearate, Sorbitol, Stearic Acid,
Tocopherol, Triethanolamine, VP/Eicosene
Copolymer, Water.